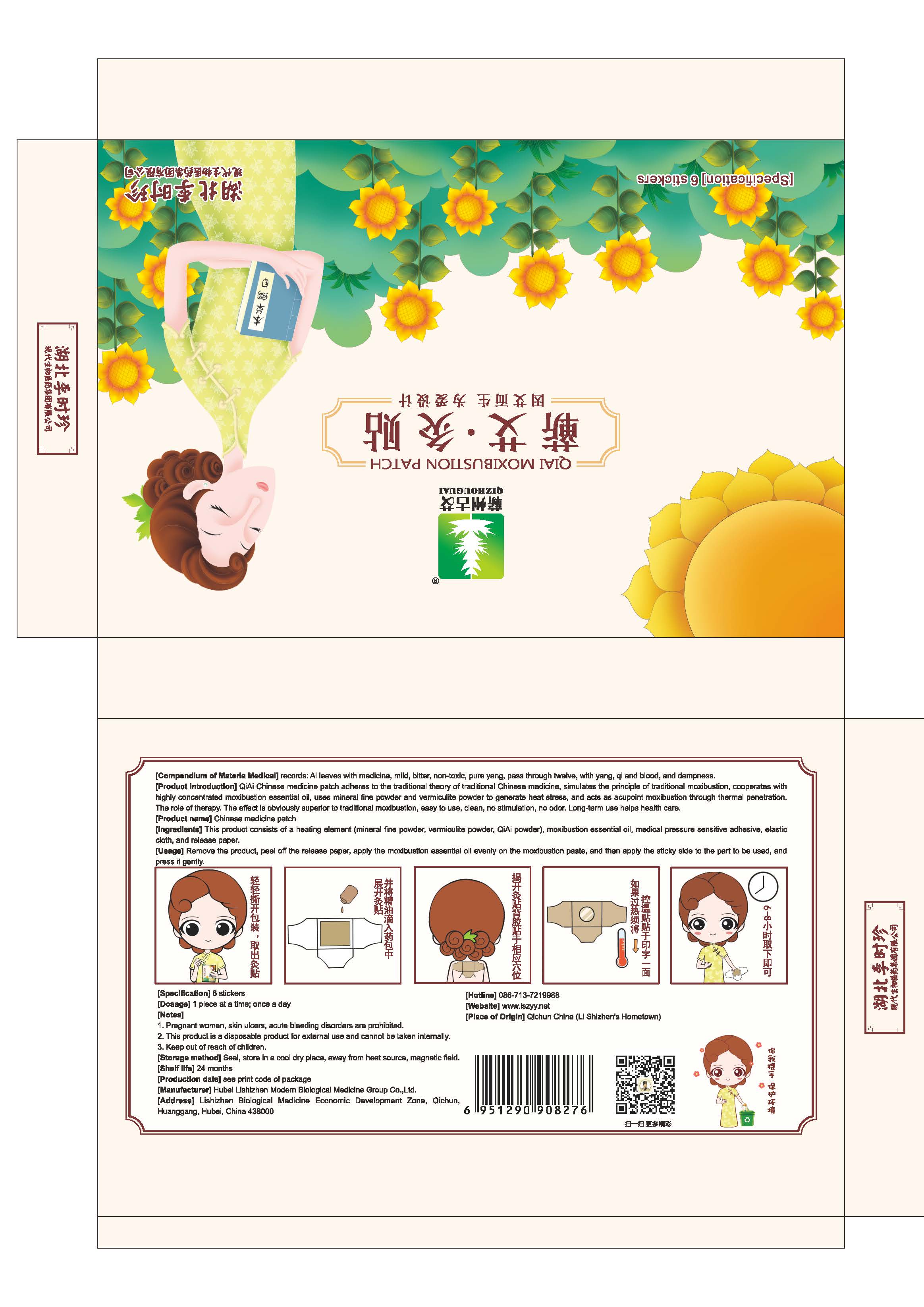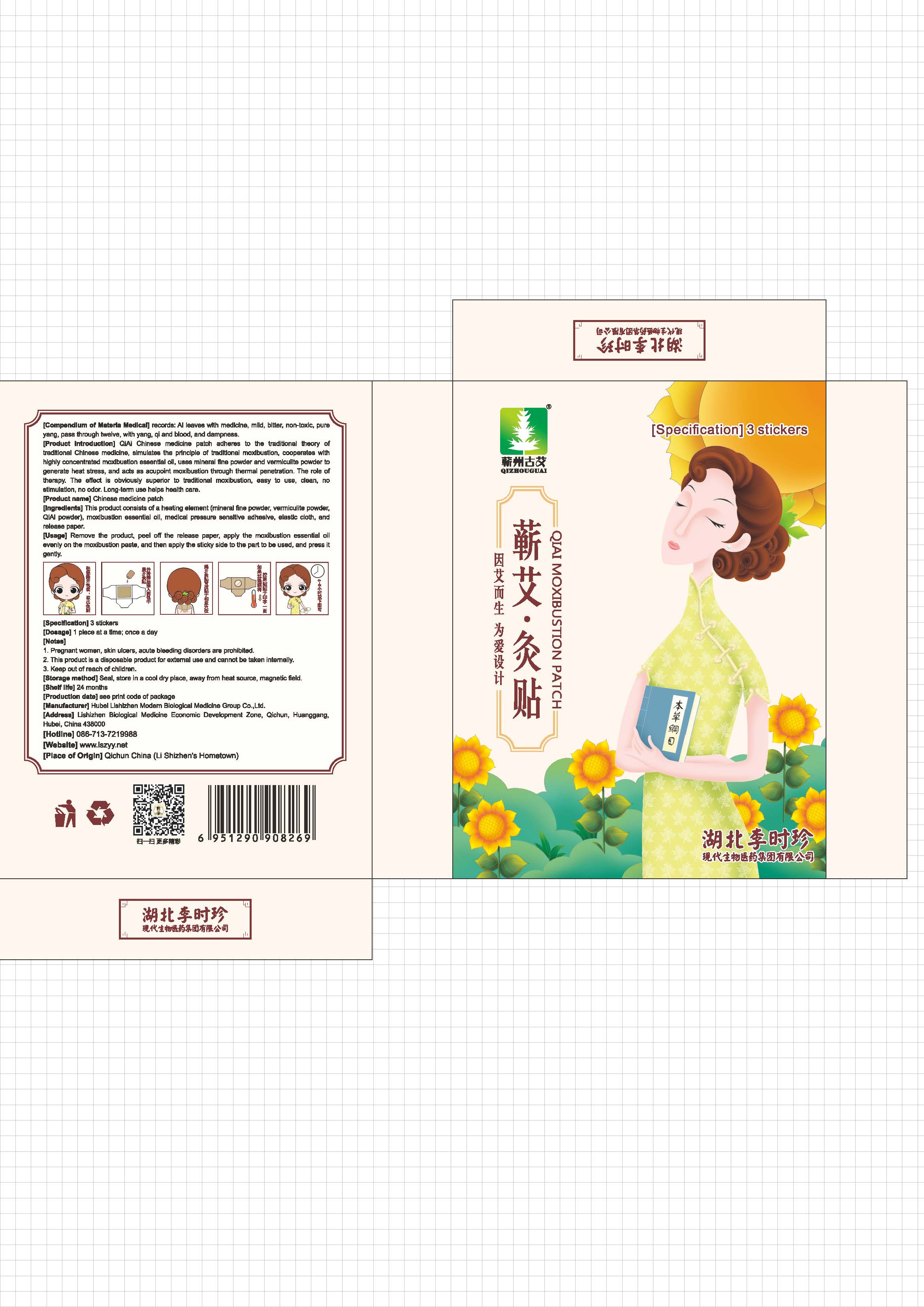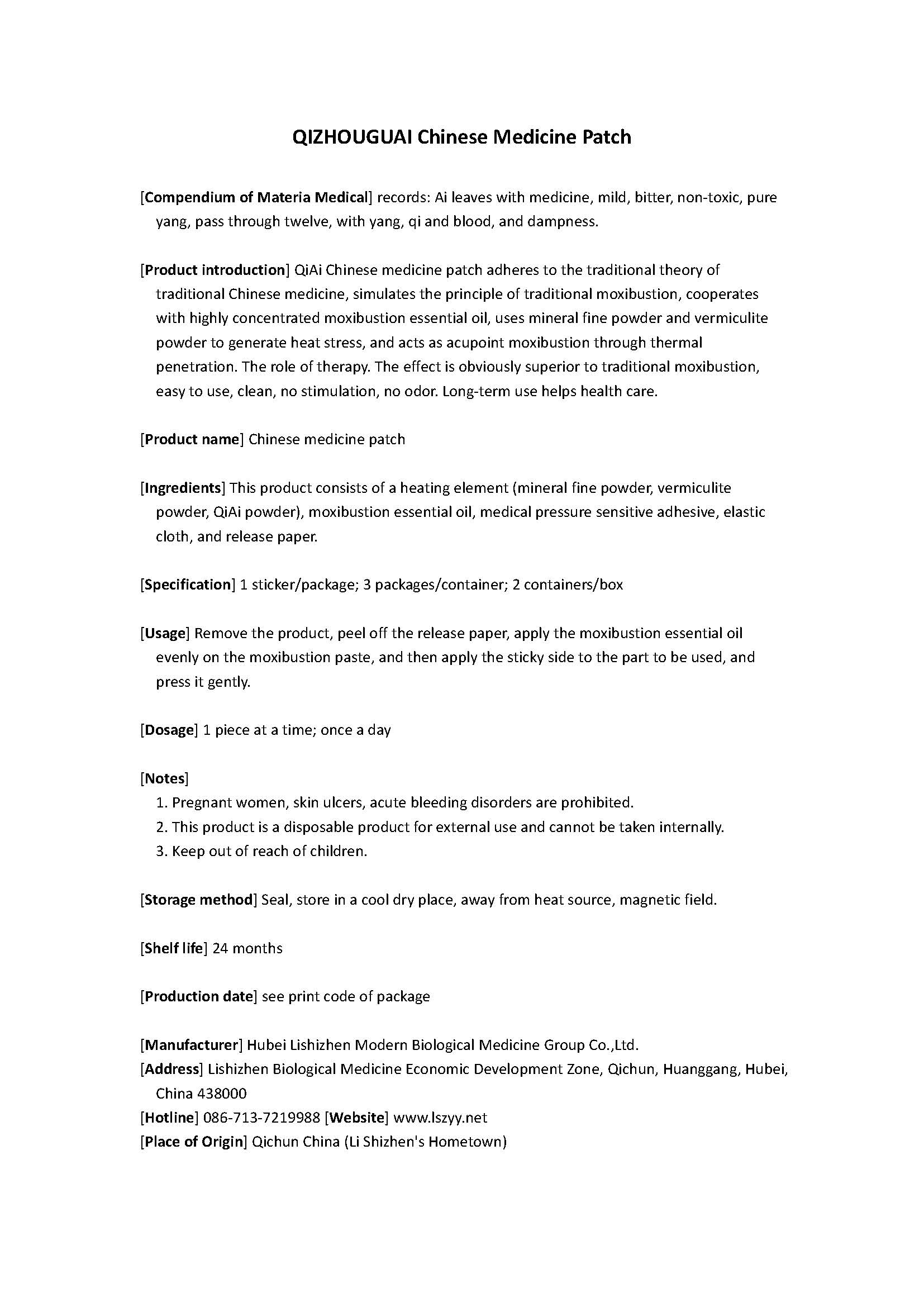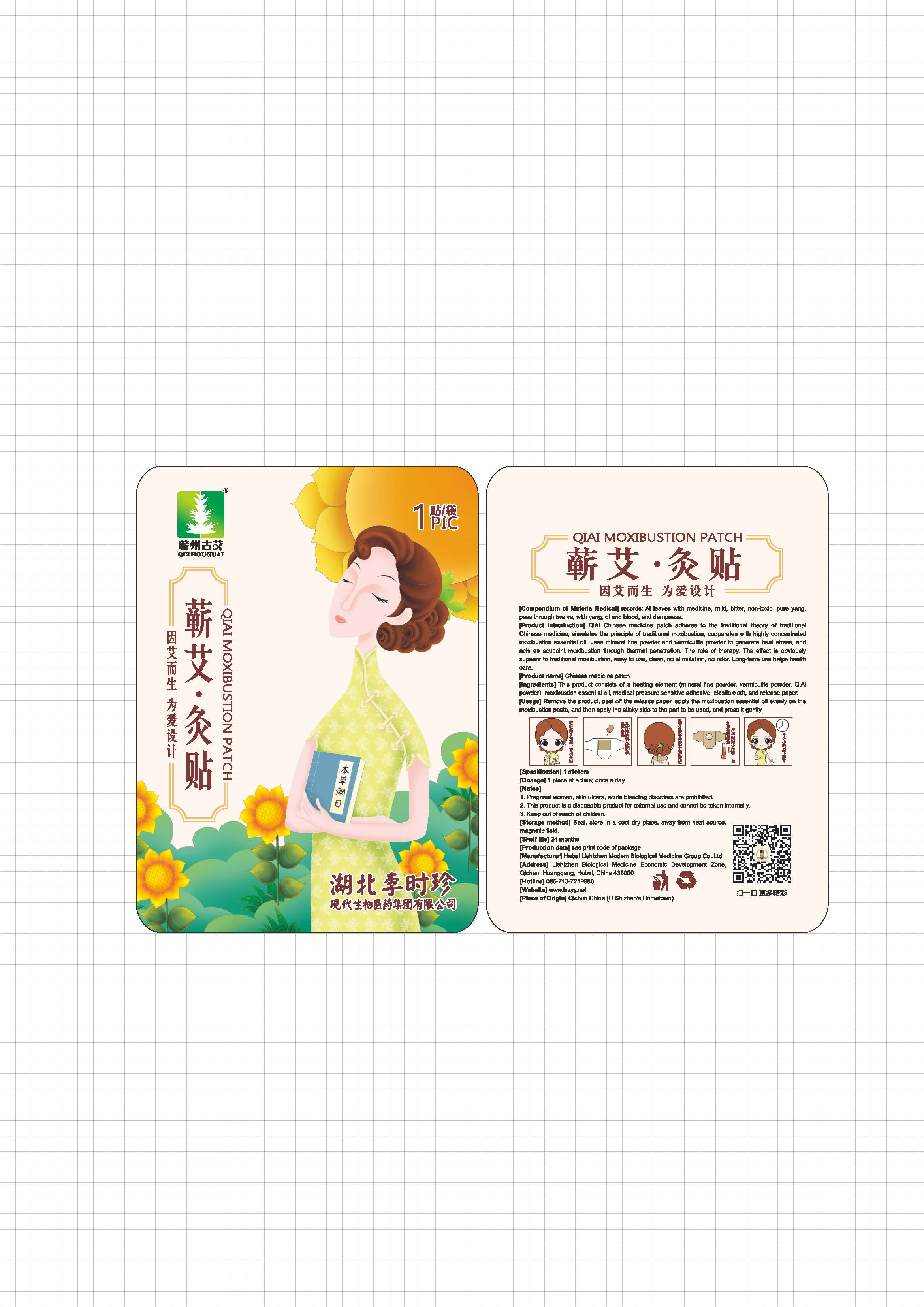 DRUG LABEL: QIZHOUGUAI Chinese medicine patch
NDC: 72624-525 | Form: TAPE
Manufacturer: Hubei Lishizhen Modern Biological Medicine Group Co.,Ltd.
Category: otc | Type: HUMAN OTC DRUG LABEL
Date: 20181023

ACTIVE INGREDIENTS: BUTYLENE GLYCOL 48 g/240 mL
INACTIVE INGREDIENTS: HYDROXYETHYL CELLULOSE (280 MPA.S AT 2%) 3.84 mL/240 mL; WATER 186.048 mL/240 mL; PHENOXYETHANOL 0.72 mL/240 mL; POLYETHYLENE GLYCOL 300000 1.2 mL/240 mL; CHLORPHENESIN 0.192 mL/240 mL

QIZHOUGUAI Chinese medicine patch, Lishizhen

Active ingredient

butylene glycol (20%): 48g/package or 48mL/package

Inactive ingredient

water (77.52%): 186.048mL/package

hydroxyethylcellulose (1.6%): 3.84mL/package

polyethylene glycol 300000 (0.5%): 1.2mL/package

phenoxyethanol (0.3%): 0.72mL/package

chlorphenesin (0.08%): 0.192mL/package

Purpose

It is a heat disposable paster incorporating chemicals that provides heat therapy for body.

When using

Conditioning neck, back, hands and feet and other rheumatism pain and spleen and stomach caused by cold injury, deficiency diarrhea and other conditions.

Do not use

If irritation or discomfort occurs, discontinue the use and consult a physician.

Stop use

If irritation or discomfort occurs, discontinue the use and consult a physician.

Ask doctor

If irritation or discomfort occurs, discontinue the use and consult a physician.

Ask doctor/pharmacist when you current use other drugs.

Keep out of reach of children and away from eyes and ears.

Questions

Please contact us when you have any questions.

Pregnancy or breast feeding

Pregnant or breast feeding women shall follow doctor advice.

Indications & usage

Pain relief, hot release, warming uterus, hemostatic, can be used to improve the conditioning neck, back, hands and feet and other rheumatism pain and spleen and stomach caused by cold injury, deficiency diarrhea and other conditions.

Apply one paster on stomach venter.

Dosage & administration

One time one paster.

Dosage forms & strengths

It is a paster.

A paster one time, or reapply as needed.

The active ingredient strength is 20%.

Warnings

If irritation or discomfort occurs, discontinue the use and consult a physician.

Very slippery on surfaces, clean spills immediately.

Keep out of reach of children and pets.

Package label. Principal display panel

Instructions

--

Package label

--

Container label

--

Box label

--